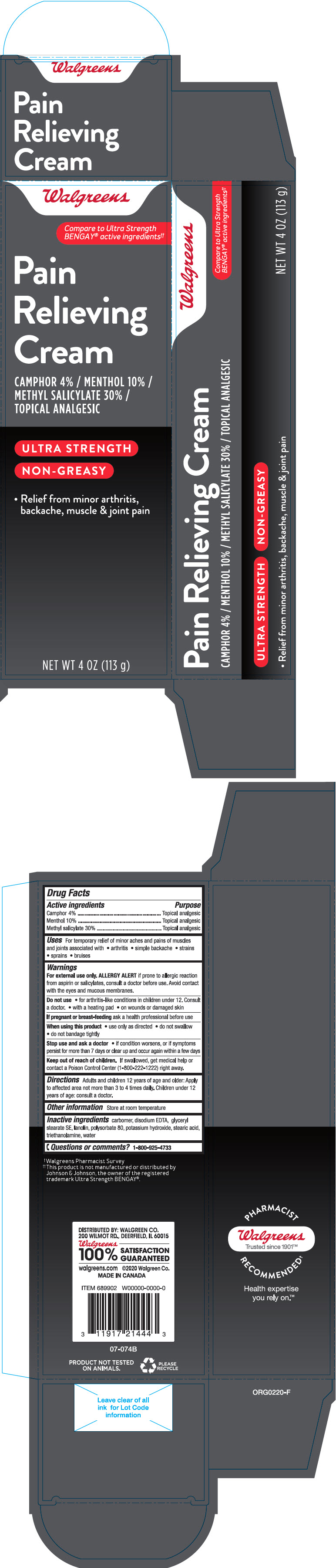 DRUG LABEL: Walgreens Pain Relieving
NDC: 0363-1199 | Form: CREAM
Manufacturer: Walgreen Company
Category: otc | Type: HUMAN OTC DRUG LABEL
Date: 20241030

ACTIVE INGREDIENTS: CAMPHOR (SYNTHETIC) 40 mg/1 g; MENTHOL, UNSPECIFIED FORM 100 mg/1 g; Methyl Salicylate 300 mg/1 g
INACTIVE INGREDIENTS: CARBOMER HOMOPOLYMER, UNSPECIFIED TYPE; EDETATE DISODIUM; Glyceryl Stearate SE; Lanolin; Polysorbate 80; Potassium Hydroxide; Stearic Acid; TROLAMINE; Water

Walgreens Pain Relieving Cream
Topical Analgesic

Drug Facts

ACTIVE INGREDIENT

Active ingredients | Purpose
Camphor 4% | Topical Analgesic
Menthol 10.0% | Topical Analgesic
Methyl Salicylate 30% | Topical Analgesic

Uses

for the temporary relief of minor aches and muscles and joints associated with

- arthritis
- simple backache
- strains
- sprains

Warnings

For external use only. ALLERGY ALERT if prone to allergic reaction from aspirin or salicylates, consult a doctor before use. Avoid contact with eyes and mucous membranes.

Do not use

- for arthritis-like conditions in children under 12. Consult a doctor.
- with a heating pad
- on wounds or damaged skin

PREGNANCY OR BREAST FEEDING

If pregnant or breast feeding ask a health professional before use

When using this product

- use only as directed
- do not swallow
- do not bandage tightly

Stop use and consult a doctor if

- condition worsens or pain lasts for more than 7 days or clear up and occur again within a few days

Keep out of reach of children. If swallowed, get medical help or contact a Poison Control Center (1-800-222-1222) right away.

Directions

- Adults and children 12 years of age and older: apply to affected area not more than 3 or 4 times daily. Children under 12 years of age: consult a doctor

Other information

Store at room temperature

Inactive ingredients

Carbomer, Disodium EDTA, Glyceryl Stearate SE, Lanolin, Polysorbate 80, Potassium Hydroxide, Stearic Acid, Triethanolamine, Water.

Questions or comments?

1-800-925-4733

DISTRIBUTED BY: WALGREEN CO.
200 WILMOT RD., DEERFIELD, IL 60015

PRINCIPAL DISPLAY PANEL - 113 g Tube Carton

Walgreens

Compare to Ultra Strength
BENGAY® active ingredients††

Pain
Relieving
Cream

CAMPHOR 4% / MENTHOL 10% /
METHYL SALICYLATE 30% /
TOPICAL ANALGESIC

ULTRA STRENGTH

NON-GREASY

- Relief from minor arthritis,
  backache, muscle & joint pain

NET WT 4 OZ (113 g)